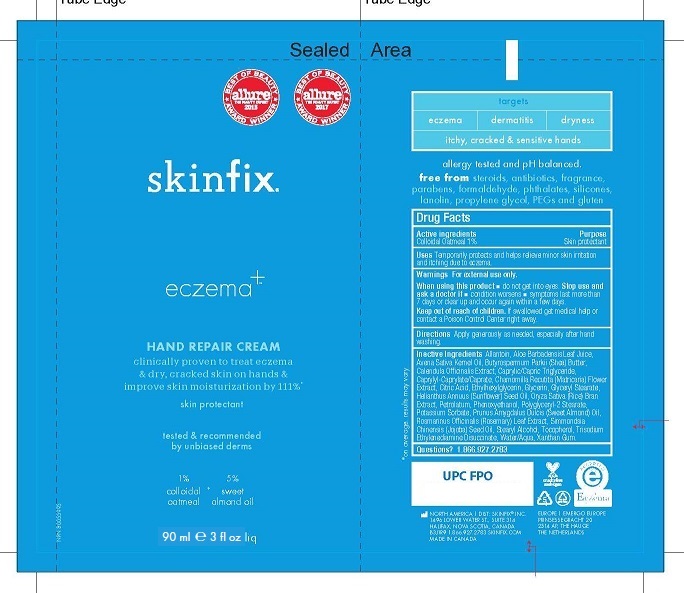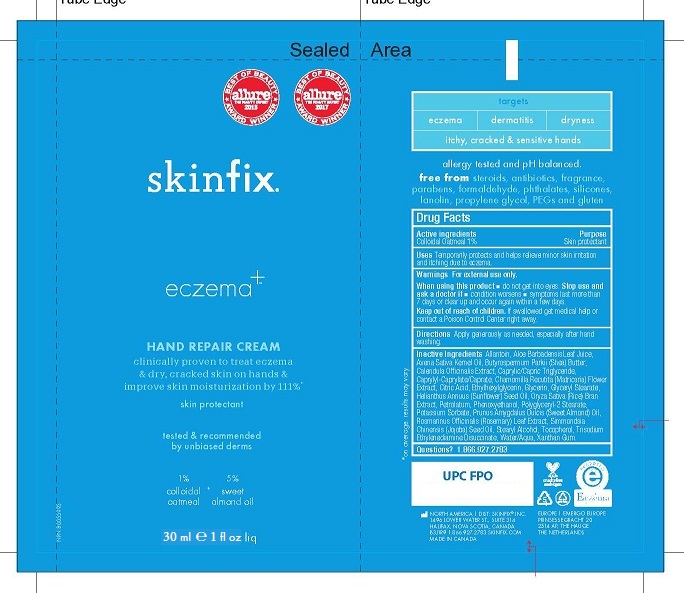 DRUG LABEL: SKINFIX HAND REPAIR
NDC: 61328-106 | Form: CREAM
Manufacturer: Skinfix, Inc.
Category: otc | Type: HUMAN OTC DRUG LABEL
Date: 20260112

ACTIVE INGREDIENTS: OATMEAL 1 g/100 mL
INACTIVE INGREDIENTS: ALLANTOIN; ALOE VERA LEAF; OAT KERNEL OIL; YELLOW WAX; SHEA BUTTER; CALENDULA OFFICINALIS WHOLE; MEDIUM-CHAIN TRIGLYCERIDES; CAPRYLYL CAPRYLATE/CAPRATE; MATRICARIA CHAMOMILLA WHOLE; ANHYDROUS CITRIC ACID; ETHYLHEXYLGLYCERIN; GLYCERIN; GLYCERYL MONOSTEARATE; SUNFLOWER OIL; ORYZA SATIVA WHOLE; PETROLATUM; PHENOXYETHANOL; POLYGLYCERYL-2 DIISOSTEARATE; POTASSIUM SORBATE; ROSMARINUS OFFICINALIS WHOLE; JOJOBA OIL; STEARYL ALCOHOL; TOCOPHEROL; TRISODIUM ETHYLENEDIAMINE DISUCCINATE; WATER; XANTHAN GUM

SKINFIX - HAND REPAIR CREAM (61328-106)

Active Ingredients

Colloidal Oatmeal 1%

Purpose

Skin Protectant

Warnings

For external use only.

When using this product Avoid contact with eyes.

Stop use and ask a doctor if condition worsens.

If symptoms last more than 7 days or clear up and occur again within a few days.

KEEP OUT OF REACH OF CHILDREN. IF SWALLOWED GET MEDICAL HELP OR CONTACT A POISON CONTROL CENTER RIGHT AWAY.

Uses

Temporarily protects dry cracked skin and helps relieve monor skin irritations and itching due to eczema.

Directions

Apply cream liberally as needed, especially after hand washing.

Inactive Ingredients:

allantoin, aloe barbadensis leaf juice, avena sativa kernel oil, beeswax, butyrospermum parkii (shea) butter, calendula officinalis extract, capyrlic/capric triglyceride, caprylyl-caprylate/caprate, chamomilla recutita (matricaria) flower extract, citric acid, ethylhexylglycerin, glyceryl stearate, helianthus annuus (sunflower) seed oil, oryza sativa (rice) bran extract, petrolatum, phenoxyethanol, polyglyceryl-2-stearate, potassium sorbate, prunus amygdalus dulcis (sweet almond) oil, rosmarinus officinalis (rosemary) leaf extract, simmondsia chinensis (jojoba) seed oil, stearyl alcohol, tocopherol, trisodium ethylenediamine disuccinate, water (aqua), xanthan gum

PACKAGE LABEL

30 ml

90 ml